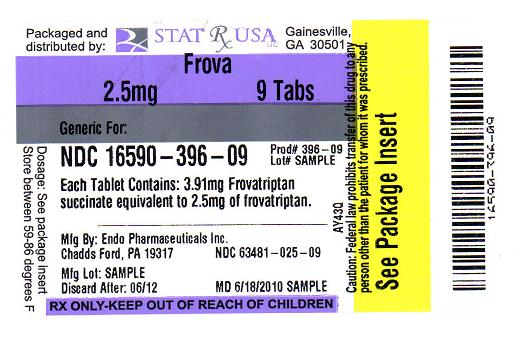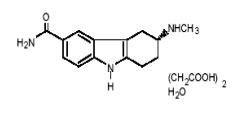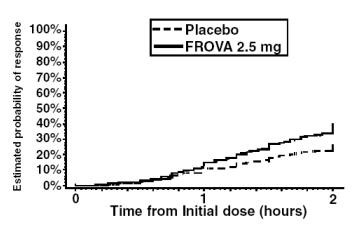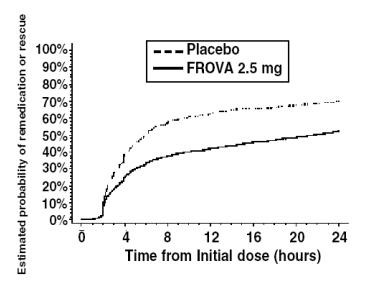 DRUG LABEL: FROVA
NDC: 16590-396 | Form: TABLET, FILM COATED
Manufacturer: STAT RX USA LLC
Category: prescription | Type: HUMAN PRESCRIPTION DRUG LABEL
Date: 20100618

ACTIVE INGREDIENTS: FROVATRIPTAN SUCCINATE 2.5 mg/1 1
INACTIVE INGREDIENTS: LACTOSE; CELLULOSE, MICROCRYSTALLINE; SILICON DIOXIDE; SODIUM STARCH GLYCOLATE TYPE A POTATO; MAGNESIUM STEARATE; HYPROMELLOSE; POLYETHYLENE GLYCOL 3000; TRIACETIN; TITANIUM DIOXIDE

FROVA®
(frovatriptan succinate) Tablets

DESCRIPTION

FROVA (frovatriptan succinate) tablets contain frovatriptan succinate, a selective 5-hydroxy-tryptamine1 (5-HT1B/1D) receptor subtype agonist, as the active ingredient. Frovatriptan succinate is chemically designated as R-(+) 3-methylamino-6-carboxamido-1,2,3,4-tetrahydrocarbazole monosuccinate monohydrate and it has the following structure:

The empirical formula is C14H17N3O.C4H6O4.H2O, representing a molecular weight of 379.4. Frovatriptan succinate is a white to off-white powder that is soluble in water. Each FROVA tablet for oral administration contains 3.91 mg frovatriptan succinate, equivalent to 2.5 mg of frovatriptan base. Each tablet also contains the inactive ingredients lactose NF, microcrystalline cellulose NF, colloidal silicon dioxide NF, sodium starch glycolate NF, magnesium stearate NF, hydroxypropylmethylcellulose USP, polyethylene glycol 3000 USP, triacetin USP, and titanium dioxide USP.

CLINICAL PHARMACOLOGY

Mechanism of Action

Frovatriptan is a 5-HT receptor agonist that binds with high affinity for 5-HT1B and 5-HT1D receptors. Frovatriptan has no significant effects on GABAA mediated channel activity and has no significant affinity for benzodiazepine binding sites.

Frovatriptan is believed to act on extracerebral, intracranial arteries and to inhibit excessive dilation of these vessels in migraine. In anesthetized dogs and cats, intravenous administration of frovatriptan produced selective constriction of the carotid vascular bed and had no effect on blood pressure (both species) or coronary resistance (in dogs).

Pharmacokinetics

Mean maximum blood concentrations (Cmax) in patients are achieved approximately 2 - 4 hours after administration of a single oral dose of frovatriptan 2.5 mg. The absolute bioavailability of an oral dose of frovatriptan 2.5 mg in healthy subjects is about 20% in males and 30% in females. Food has no significant effect on the bioavailability of frovatriptan, but delays tmax by one hour.

Binding of frovatriptan to serum proteins is low (approximately 15%). Reversible binding to blood cells at equilibrium is approximately 60%, resulting in a blood:plasma ratio of about 2:1 in both males and females. The mean steady state volume of distribution of frovatriptan following intravenous administration of 0.8 mg is 4.2 L/kg in males and 3.0 L/kg in females.

In vitro, cytochrome P450 1A2 appears to be the principal enzyme involved in the metabolism of frovatriptan. Following administration of a single oral dose of radiolabeled frovatriptan 2.5 mg to healthy male and female subjects, 32% of the dose was recovered in urine and 62% in feces. Radiolabeled compounds excreted in urine were unchanged frovatriptan, hydroxylated frovatriptan, N-acetyl desmethyl frovatriptan, hydroxylated N-acetyl desmethyl frovatriptan and desmethyl frovatriptan, together with several other minor metabolites. Desmethyl frovatriptan has lower affinity for 5-HT1B/1D receptors compared to the parent compound. The N-acetyl desmethyl metabolite has no significant affinity for 5-HT receptors. The activity of the other metabolites is unknown.

After an intravenous dose, mean clearance of frovatriptan was 220 and 130 mL/min in males and females, respectively. Renal clearance accounted for about 40% (82 mL/min) and 45% (60 mL/min) of total clearance in males and females, respectively. The mean terminal elimination half-life of frovatriptan in both males and females is approximately 26 hours.

The pharmacokinetics of frovatriptan are similar in migraine patients and healthy subjects.

Special Populations

Age:

Mean AUC of frovatriptan was 1.5- to 2-fold higher in healthy elderly subjects (age 65 – 77 years) compared to those in healthy younger subjects (age 21 - 37 years). There was no difference in tmax or t1/2 between the two populations.

Gender:

There was no difference in the mean terminal elimination half-life of frovatriptan in males and females. Bioavailability was higher, and systemic exposure to frovatriptan was approximately 2-fold greater, in females than males, irrespective of age.

Renal Impairment:

Since less than 10% of FROVA is excreted in urine after an oral dose, it is unlikely that the exposure to frovatriptan will be affected by renal impairment. The pharmacokinetics of frovatriptan following a single oral dose of 2.5 mg was not different in patients with renal impairment (5 males and 6 females, creatinine clearance 16 - 73 mL/min) and in subjects with normal renal function.

Hepatic Impairment:

There is no clinical or pharmacokinetic experience with FROVA in patients with severe hepatic impairment. The AUC in subjects with mild (Child-Pugh 5 - 6) to moderate (Child-Pugh 7 - 9) hepatic impairment is about twice as high as the AUC in young, healthy subjects, but within the range found among normal elderly subjects.

Race:

The effect of race on the pharmacokinetics of frovatriptan has not been examined.

Drug Interactions (see also PRECAUTIONS, Drug Interactions)

Frovatriptan is not an inhibitor of human monoamine oxidase (MAO) enzymes or cytochrome P450 (isozymes 1A2, 2C9, 2C19, 2D6, 2E1, 3A4) in vitro at concentrations up to 250 to 500- fold higher than the highest blood concentrations observed in man at a dose of 2.5 mg. No induction of drug metabolizing enzymes was observed following multiple dosing of frovatriptan to rats or on addition to human hepatocytes in vitro. Although no clinical studies have been performed, it is unlikely that frovatriptan will affect the metabolism of co-administered drugs metabolized by these mechanisms.

Oral contraceptives:

Retrospective analysis of pharmacokinetic data from females across trials indicated that the mean Cmax and AUC of frovatriptan are 30% higher in those subjects taking oral contraceptives compared to those not taking oral contraceptives.

Ergotamine:

The AUC and Cmax of frovatriptan (2 x 2.5 mg dose) were reduced by approximately 25% when co-administered with ergotamine tartrate.

Propranolol:

Propranolol increased the AUC of frovatriptan 2.5 mg in males by 60% and in females by 29%. The Cmax of frovatriptan was increased 23% in males and 16% in females in the presence of propranolol. The tmax as well as half-life of frovatriptan, though slightly longer in the females, were not affected by concomitant administration of propranolol.

Moclobemide:

The pharmacokinetic profile of frovatriptan was unaffected when a single oral dose of frovatriptan 2.5 mg was administered to healthy female subjects receiving the MAO-A inhibitor, moclobemide, at an oral dose of 150 mg bid for 8 days.

Clinical Trials

The efficacy of FROVA in the acute treatment of migraine headaches was demonstrated in five randomized, double-blind, placebo-controlled, outpatient trials. Two of these were dose-finding studies in which patients were randomized to receive doses of frovatriptan ranging from 0.5 - 40 mg. The three studies evaluating only one dose studied 2.5 mg. In these controlled short-term studies combined, patients were predominately female (88%) and Caucasian (94%) with a mean age of 42 years (range 18 - 69). Patients were instructed to treat a moderate to severe headache. Headache response, defined as a reduction in headache severity from moderate or severe pain to mild or no pain, was assessed for up to 24 hours after dosing. The associated symptoms nausea, vomiting, photophobia and phonophobia were also assessed. Maintenance of response was assessed for up to 24 hours post dose. In two of the trials a second dose of FROVA was provided after the initial treatment, to treat recurrence of the headache within 24 hours. Other medication, excluding other 5-HT1 agonists and ergotamine containing compounds, was permitted from 2 hours after the first dose of FROVA. The frequency and time to use of additional medications were also recorded.

In all five placebo-controlled trials, the percentage of patients achieving a headache response 2 hours after treatment was significantly greater for those taking FROVA compared to those taking placebo (Table 1).

Lower doses of frovatriptan (1 mg or 0.5 mg) were not effective at 2 hours. Higher doses (5 mg to 40 mg) of frovatriptan showed no added benefit over 2.5 mg but did cause a greater incidence of adverse events.

Table 1 Percentage of Patients with Headache Response (Mild or No Headache) 2 Hours Following Treatmenta
Trial | FROVA (frovatriptan 2.5 mg) | Placebo
1 | 42%* (n=90) | 22% (n=91)
2 | 38%* (n=121) | 25% (n=115)
3 | 39%* (n=187) | 21% (n=99)
4 | 46%** (n=672) | 27% (n=347)
5 | 37%** (n=438) | 23% (n=225)
aITT observed data, excludes patients who had missing data or were asleep;
*p<0.05,
**p<0.001 in comparison with placebo

Comparisons of drug performance based upon results obtained in different clinical trials are never reliable. Because trials are conducted at different times, with different samples of patients, by different investigators, employing different criteria and/or different interpretations of the same criteria, under different conditions (dose, dosing regimen, etc.), quantitative estimates of treatment response and the timing of response may be expected to vary considerably from study to study.

The estimated probability of achieving an initial headache response by 2 hours following treatment is depicted in Figure 1.

Figure 1

Estimated Probability of Achieving Initial Headache Response Within 2 Hours

Figure 1 shows a Kaplan-Meier plot of the probability over time of obtaining headache response (no or mild pain) following treatment with frovatriptan 2.5 mg or placebo. The probabilities displayed are based on pooled data from four placebo-controlled trials described in Table 1(Trials 1, 3, 4 and 5). Patients who did not achieve a response were censored at 24 hours.

In patients with migraine-associated nausea, photophobia and phonophobia at baseline there was a decreased incidence of these symptoms in FROVA treated patients compared to placebo. The estimated probability of patients taking a second dose or other medication for their migraine over the 24 hours following the initial dose of study treatment is summarized in Figure 2.

Figure 2

Estimated Probability of Patients Taking a Second Dose or Other Medication for Migraine Over the 24 Hours Following the Initial Dose of Study Treatment

Figure 2 is a Kaplan-Meier plot showing the probability of patients taking a second dose or other medication for migraine over the 24 hours following the initial dose of study medication based on the data from four placebo-controlled trials described in Table 1 (Trials 1, 3, 4 and 5). The plot includes those patients who had a response to the initial dose and those who did not. The protocols did not permit remedication within 2 hours of the initial dose.

Efficacy was unaffected by a history of aura; gender; age, or concomitant medications commonly used by migraine patients FROVA.

INDICATIONS AND USAGE

FROVA is indicated for the acute treatment of migraine attacks with or without aura in adults.

FROVA is not intended for the prophylactic therapy of migraine or for use in the management of hemiplegic or basilar migraine (see CONTRAINDICATIONS). The safety and effectiveness of FROVA have not been established for cluster headache, which is present in an older, predominately male, population.

CONTRAINDICATIONS

FROVA should not be given to patients with ischemic heart disease (e.g. angina pectoris, history of myocardial infarction, or documented silent ischemia), or to patients who have symptoms or findings consistent with ischemic heart disease, coronary artery vasospasm, including Prinzmetal’s variant angina or other significant underlying cardiovascular disease (see WARNINGS).

FROVA should not be given to patients with cerebrovascular syndromes including (but not limited to) strokes of any type as well as transient ischemic attacks.

FROVA should not be given to patients with peripheral vascular disease including (but is not limited to) ischemic bowel disease (see WARNINGS)

FROVA should not be given to patients with uncontrolled hypertension (see WARNINGS).

FROVA should not be administered to patients with hemiplegic or basilar migraine.

FROVA should not be used within 24 hours of treatment with another 5-HT1 agonist, an ergotamine containing or ergot-type medication such as dihydroergotamine (DHE) or methysergide.

FROVA is contraindicated in patients who are hypersensitive to frovatriptan or any of the inactive ingredients in the tablets.

WARNINGS

FROVA should only be used where a clear diagnosis of migraine has been established.

Risk of Myocardial Ischemia and/or Infarction and Other Adverse Cardiac Events:

Because of the potential of this class of compound (5-HT1 agonists) to cause coronary vasospasm, frovatriptan should not be given to patients with documented ischemic or vasospastic coronary artery disease (CAD) (see CONTRAINDICATIONS). It is strongly recommended that frovatriptan not be given to patients in whom unrecognized CAD is predicted by the presence of risk factors (e.g., hypertension, hypercholesterolemia, smoker, obesity, diabetes, strong family history of CAD, female with surgical or physiological menopause, or male over 40 years of age) unless a cardiovascular evaluation provides satisfactory clinical evidence that the patient is reasonably free of coronary artery and ischemic myocardial disease or other significant underlying cardiovascular disease. The sensitivity of cardiac diagnostic procedures to detect cardiovascular disease or predisposition to coronary artery vasospasm is modest, at best. If, during the cardiovascular evaluation, the patient’s medical history, electrocardiographic, or other investigations reveal findings indicative of, or consistent with, coronary artery vasospasm or myocardial ischemia, frovatriptan should not be administered (see CONTRAINDICATIONS).

For patients with risk factors predictive of CAD, who are determined to have a satisfactory cardiovascular evaluation, it is strongly recommended that administration of the first dose of frovatriptan take place in the setting of a physician’s office or similar medically staffed and equipped facility unless the patient has previously received frovatriptan. Because cardiac ischemia can occur in the absence of clinical symptoms, consideration should be given to obtaining on the first occasion of use an electrocardiogram (ECG) during the interval immediately following administration of FROVA in these patients with risk factors.

It is recommended that patients who are intermittent long-term users of 5-HT1 agonists, including FROVA and who have or acquire risk factors predictive of CAD, as described above, undergo periodic cardiovascular evaluation as they continue to use FROVA.

The systematic approach described above is intended to reduce the likelihood that patients with unrecognized cardiovascular disease would be inadvertently exposed to frovatriptan.

Cardiac Events and Fatalities with 5-HT1 Agonists:

Serious adverse cardiac events, including acute myocardial infarction, life-threatening disturbances of cardiac rhythm and death have been reported within a few hours of administration of 5-HT1 agonists. Considering the extent of use of 5-HT1 agonists in patients with migraine, the incidence of these events is extremely low.

Premarketing experience with frovatriptan:

Among more than 3000 patients with migraine who participated in premarketing clinical trials of FROVA no deaths or serious cardiac events were reported which were related to the use of FROVA.

Cerebrovascular Events and Fatalities with 5-HT1 Agonists:

Cerebral hemorrhage, subarachnoid hemorrhage, stroke and other cerebrovascular events have been reported in patients treated with 5-HT1 agonists; and some have resulted in fatalities. In a number of cases, it appears possible that the cerebrovascular events were primary, the agonist having been administered in the incorrect belief that the symptoms experienced were a consequence of migraine, when they were not. It should be noted that patients with migraine may be at increased risk of certain cerebrovascular events (e.g. stroke, hemorrhage, transient ischemic attack).

Other Vasospasm-Related Events:

5-HT1 agonists may cause vasospastic reactions other than coronary artery spasm. Both peripheral vascular ischemia and colonic ischemia with abdominal pain and bloody diarrhea have been reported with 5-HT1 agonists.

Effects on Blood Pressure:

In young healthy subjects, there were statistically significant increases in systolic and diastolic blood pressure after single doses of 80 mg frovatriptan (32 times the clinical dose) and above. These increases were transient, resolved spontaneously and were not clinically significant. At the recommended dose of 2.5 mg, transient changes in systolic blood pressure were recorded in some elderly subjects (65 - 77 years). Any increases were generally small, resolved spontaneously, and blood pressure remained within the normal range. Frovatriptan is contraindicated in patients with uncontrolled hypertension (see CONTRAINDICATIONS).

An 18% increase in mean pulmonary artery pressure was seen following dosing with another 5-HT1 agonist in a study evaluating subjects undergoing cardiac catheterization.

Serotonin Syndrome:

The development of a potentially life-threatening serotonin syndrome may occur with triptans, including FROVA treatment, particularly during combined use with selective serotonin reuptake inhibitors (SSRIs) or serotonin norepinephrine reuptake inhibitors (SNRIs). If concomitant treatment with FROVA and an SSRI (e.g., fluoxetine, paroxetine, sertraline, fluvoxamine, citalopram, escitalopram) or SNRI (e.g., venlafaxine, duloxetine) is clinically warranted, careful observation of the patient is advised, particularly during treatment initiation and dose increases. Serotonin syndrome symptoms may include mental status changes (e.g., agitation hallucinations, coma), autonomic instability (e.g., tachycardia, labile blood pressure, hyperthermia), neuromuscular aberrations (e.g., hyperreflexia, incoordination) and/or gastrointestinal symptoms (e.g., nausea, vomiting, diarrhea). (See PRECAUTIONS – Drug Interactions).

PRECAUTIONS

General:

As with other 5-HT1 agonists, sensations of pain, tightness, pressure and heaviness have been reported in the chest, throat, neck and jaw after treatment with FROVA. These events have not been associated with arrhythmias or ischemic ECG changes in clinical trials with FROVA. Because 5-HT1 agonists may cause coronary vasospasm, patients who experience signs or symptoms suggestive of angina following dosing should be evaluated for the presence of CAD. Patients shown to have CAD and those with Prinzmetal’s variant angina should not receive 5-HT1 agonists (see CONTRAINDICATIONS). Patients who experience other symptoms or signs suggestive of decreased arterial flow, such as ischemic bowel syndrome or Raynaud’s syndrome following the use of any 5-HT1 agonist are candidates for further evaluation. If a patient has no response for the first migraine attack treated with FROVA, the diagnosis of migraine should be reconsidered before frovatriptan is administered to treat any subsequent attacks.

Hepatically Impaired Patients:

There is no clinical or pharmacokinetic experience with FROVA in patients with severe hepatic impairment. The AUC of frovatriptan in patients with mild (Child-Pugh 5-6) to moderate (Child-Pugh 7-9) hepatic impairment was about twice that of young, healthy subjects, but within the range observed in healthy elderly subjects and was considerably lower than the values attained with higher doses of frovatriptan (up to 40 mg), which were not associated with any serious adverse effects. Therefore, no dosage adjustment is necessary when FROVA is given to patients with mild to moderate hepatic impairment (see CLINICAL PHARMACOLOGY, Special Populations).

Binding to Melanin-Containing Tissues:

When pigmented rats were given a single oral dose of 5 mg/kg of radiolabeled frovatriptan, the radioactivity in the eye after 28 days was 87% of the value measured after 8 hours. This suggests that frovatriptan and/or its metabolites may bind to the melanin of the eye. Because there could be accumulation in melanin rich tissues over time, this raises the possibility that frovatriptan could cause toxicity in these tissues after extended use. However, no effects on the retina related to treatment with frovatriptan were noted in the toxicity studies. Although no systematic monitoring of ophthalmologic function was undertaken in clinical trials and no specific recommendations for ophthalmologic monitoring are made, prescribers should be aware of the possibility of long-term ophthalmologic effects.

Information for Patients

Physicians should instruct their patients to read the patient package insert before taking FROVA. See PATIENT INFORMATION at the end of this labeling for the text of the separate leaflet provided for patients.

Patients should be cautioned about the risk of serotonin syndrome with the use of FROVA or other triptans, especially during combined use with selective serotonin reuptake inhibitors (SSRIs) or serotonin norepinephrine reuptake inhibitors (SNRIs).

Laboratory Tests

No specific laboratory tests are recommended for monitoring patients prior to and/or after treatment with FROVA.

Drug Interactions (see also CLINICAL PHARMACOLOGY, Drug Interactions)

Ergot-containing drugs have been reported to cause prolonged vasospastic reactions. Due to a theoretical risk of a pharmacodynamic interaction, use of ergotamine-containing or ergot-type medications (like dihydroergotamine or methysergide) and FROVA within 24 hours of each other should be avoided (see CONTRAINDICATIONS).

Concomitant use of other 5HT1B/1D agonists within 24 hours of FROVA treatment is not recommended (see CONTRAINDICATIONS).

Selective Serotonin Reuptake Inhibitors / Serotonin Norepinephrine Reuptake Inhibitors and Serotonin Syndrome: Cases of life-threatening serotonin syndrome have been reported during combined use of selective serotonin reuptake inhibitors (SSRIs) or serotonin norepinephrine reuptake inhibitors (SNRIs) and triptans. (See WARNINGS).

Drug/Laboratory Test Interactions

FROVA is not known to interfere with commonly employed clinical laboratory tests.

Carcinogenesis, Mutagenesis, Impairment of Fertility

Carcinogenesis: The carcinogenic potential of frovatriptan was evaluated in an 84-week study in mice (4, 13, and 40 mg/kg/day), a 104-week study in rats (8.5, 27 and 85 mg/kg/day), and a 26-week study in p53(+/-) transgenic mice (20, 62.5, 200, and 400 mg/kg/day). Although the maximum tolerated dose (MTD) was not achieved in the 84-week mouse study and in female rats, exposures at the highest doses studied were many fold greater than those achieved at the maximum recommended daily human dose (MRHD) of 7.5 mg. There were no increases in tumor incidence in the 84-week mouse study at doses producing 140 times the exposure achieved at the MRHD based on blood AUC comparisons. In the rat study, there was a statistically significant increase in the incidence of pituitary adenomas in males only at 85 mg/kg/day, a dose that produced 250 times the exposure achieved at the MRHD based on AUC comparisons. In the 26-week p53(+/-) transgenic mouse study, there was an increased incidence of subcutaneous sarcomas in females dosed at 200 and 400 mg/kg/day, or 390 and 630 times the human exposure based on AUC comparisons. The incidence of sarcomas was not increased at lower doses that achieved exposures 180 and 60 times the human exposure. These sarcomas were physically associated with subcutaneously implanted animal identification transponders. There were no other increases in tumor incidence of any type in any dose group. These sarcomas are not considered to be relevant to humans.

Mutagenesis: Frovatriptan was clastogenic in human lymphocyte cultures,in the absence of metabolic activation. In the bacterial reverse mutation assay (Ames test), frovatriptan produced an equivocal response in the absence of metabolic activation. No mutagenic or clastogenic activities were seen in an in vitro mouse lymphoma assay, an in vivo mouse bone marrow micronucleus test, or an ex vivo assay for unscheduled DNA synthesis in rat liver.

Impairment of Fertility: Male and female rats were dosed prior to and during mating, and up to implantation, at doses of 100, 500, and 1000 mg/kg/day (equivalent to approximately 130, 650, and 1300 times the MRHD on a mg/m^2 basis). At all dose levels there was an increase in the number of females that mated on the first day of pairing compared to control animals. This occurred in conjunction with a prolongation of the estrous cycle. In addition females had a decreased mean number of corpora lutea, and consequently a lower number of live fetuses per litter, which suggested a partial impairment of ovulation. There were no other fertility-related effects.

Pregnancy: Pregnancy Category C

When pregnant rats were administered frovatriptan during the period of organogenesis at oral doses of 100, 500 and 1000 mg/kg/day (equivalent to 130, 650 and 1300 times the maximum recommended human dose [MRHD] on a mg/m^2 basis) there were dose related increases in incidences of both litters and total numbers of fetuses with dilated ureters, unilateral and bilateral pelvic cavitation, hydronephrosis, and hydroureters. A no-effect dose for renal effects was not established. This signifies a syndrome of related effects on a specific organ in the developing embryo in all treated groups, which is consistent with a slight delay in fetal maturation. This delay was also indicated by a treatment related increased incidence of incomplete ossification of the sternebrae, skull and nasal bones in all treated groups. Slightly lower fetal weights and an increased incidence of early embryonic deaths in treated rats were observed; although not statistically significant compared to control, the latter effect occurred in both the embryo-fetal developmental study and in the prenatal-postnatal developmental study. There was no evidence of this latter effect at the lowest dose level studied, 100 mg/kg/day (equivalent to 130 times the MRHD on a mg/m^2 basis). When pregnant rabbits were dosed throughout organogenesis at doses up to 80 mg/kg/day (equivalent to 210 times the MRHD on a mg/m^2 basis) no effects on fetal development were observed.

There are no adequate and well-controlled studies in pregnant women; therefore, frovatriptan should be used during pregnancy only if the potential benefit justifies the potential risk to the fetus.

Nursing Mothers

It is not known whether frovatriptan is excreted in human milk. Frovatriptan and/or its metabolites are excreted in the milk of lactating rats with the maximum concentration being four-fold higher than that seen in blood. Therefore, caution should be exercised when considering the administration of FROVA to a nursing woman.

Pediatric Use

Safety and effectiveness of FROVA in pediatric patients have not been established; therefore, FROVA is not recommended for use in patients under 18 years of age. Postmarketing experience with other triptans includes a limited number of reports that describe pediatric patients who have experienced clinically serious adverse events that are similar in nature to those reported rarely in adults.

Use in the Elderly

Mean blood concentrations of frovatriptan in elderly subjects were 1.5- to 2-times higher than those seen in younger adults (see CLINICAL PHARMACOLOGY, Special Populations). Because migraine occurs infrequently in the elderly, clinical experience with FROVA is limited in such patients.

ADVERSE REACTIONS

Serious cardiac events, including some that have been fatal, have occurred following use of 5-HT1 agonists. These events are extremely rare and most have been reported in patients with risk factors predictive of CAD. Events reported have included coronary artery vasospasm, transient myocardial ischemia, myocardial infarction, ventricular tachycardia and ventricular fibrillation (see CONTRAINDICATIONS, WARNINGS and PRECAUTIONS).

Incidence in Controlled Clinical Trials:

Among 1554 patients treated with FROVA in four placebo-controlled trials (Trials 1, 3, 4 and 5 in Table 1), only 1% (16) patients withdrew because of treatment-emergent adverse events. In a long term, open-label study where patients were allowed to treat multiple migraine attacks with FROVA for up to 1 year, 5% (26/496) patients discontinued due to treatment-emergent adverse events.

The treatment-emergent adverse events that occurred most frequently following administration of frovatriptan 2.5 mg (i.e., in at least 2% of patients), and at an incidence ≥1% greater than with placebo, in the four placebo-controlled trials were dizziness, paresthesia, headache, dry mouth, fatigue, flushing, hot or cold sensation and chest pain.

Table 2 lists treatment-emergent adverse events reported within 48 hours of drug administration that occurred with frovatriptan 2.5 mg at an incidence of ≥ 2% and more often than on placebo, in the first attack in four placebo-controlled trials (Trials 1, 3, 4 and 5 in Table 1). These studies involved 2392 patients (1554 frovatriptan 2.5 mg and 838 placebo). The events cited reflect experience gained under closely monitored conditions of clinical trials in a highly selected patient population. In actual clinical practice or in other clinical trials, these incidence estimates may not apply, as the conditions of use, reporting behavior, and the kinds of patients treated may differ.

Table 2: Treatment-Emergent Adverse Events (Incidence ≥ 2% and Greater Than Placebo) of Patients in Four Placebo-Controlled Migraine Trials
Adverse events | Frovatriptan 2.5 mg (n=1554) | Placebo (n=838)
Central & peripheral nervous system; Dizziness; Headache; Paresthesia | 8%; 4%; 4% | 5%; 3%; 2%
Gastrointestinal system disorders; Mouth dry; Dyspepsia | 3%; 2% | 1%; 1%
Body as a whole – general disorders; Fatigue; Hot or cold sensation; Chest pain | 5%; 3%; 2% | 2%; 2%; 1%
Musculo-skeletal; Skeletal pain | 3% | 2%
Vascular; Flushing | 4% | 2%

Other events that occurred at ≥2% on frovatriptan that were equally or more common in the placebo group were somnolence and nausea.

FROVA is generally well tolerated. The incidence of adverse events in clinical trials did not increase when up to 3 doses were used within 24 hours. The majority of adverse events were mild or moderate and transient. The incidence of adverse events in four placebo-controlled clinical trials was not affected by gender, age or concomitant medications commonly used by migraine patients. There were insufficient data to assess the impact of race on the incidence of adverse events.

Other Events Observed in Association with FROVA:

In the paragraphs that follow, the incidence of less commonly reported adverse events in four placebo-controlled trials are presented. Variability associated with adverse event reporting, the terminology used to describe adverse events etc, limit the value of the incidence estimates provided. The incidence of each adverse event is calculated as the number of patients reporting the event at least once divided by the number of patients who used FROVA. All adverse events reported within 48 hours of drug administration in the first attack in four placebo controlled trials involving 2392 patients (1554 frovatriptan 2.5 mg and 838 placebo) are included, except those already listed in Table 2, those too general to be informative, those not reasonably associated with the use of the drug and those which occurred at the same or a greater incidence in the placebo group. Events are further classified within body system categories and enumerated in order of decreasing frequency using the following definitions: frequent adverse events are those occurring in at least 1/100 patients, infrequent adverse events are those occurring in between 1/100 and 1/1000 patients, and rare adverse events are those occurring in fewer than 1/1000 patients.

Central and peripheral nervous system: Frequent: dysesthesia and hypoesthesia. Infrequent: tremor, hyperesthesia, migraine aggravated, involuntary muscle contractions, vertigo, ataxia, abnormal gait and speech disorder. Rare: hypertonia, hypotonia, abnormal reflexes and tongue paralysis.

Gastrointestinal: Frequent: vomiting, abdominal pain and diarrhea. Infrequent: dysphagia, flatulence, constipation, anorexia, esophagospasm and saliva increased. Rare: change in bowel habits, cheilitis, eructation, gastroesophageal reflux, hiccup, peptic ulcer, salivary gland pain, stomatitis and toothache.

Body as a whole: Frequent: pain. Infrequent: asthenia, rigors, fever, hot flushes and malaise. Rare: feeling of relaxation, leg pain and edema mouth.

Psychiatric: Frequent: insomnia and anxiety. Infrequent: confusion, nervousness, agitation, euphoria, impaired concentration, depression, emotional lability, amnesia, thinking abnormal and depersonalization. Rare: depression aggravated, abnormal dreaming and personality disorder.

Musculoskeletal: Infrequent: myalgia, back pain, arthralgia, arthrosis, leg cramps and muscle weakness.

Respiratory: Frequent: sinusitis and rhinitis. Infrequent: pharyngitis, dyspnea, hyperventilation and laryngitis.

Vision disorders: Frequent: vision abnormal. Infrequent: eye pain, conjunctivitis and abnormal lacrimation.

Skin and appendages: Frequent: sweating increased. Infrequent: pruritis, and bullous eruption.

Hearing and vestibular disorders: Frequent: tinnitus. Infrequent: ear ache, and hyperacusis.

Heart rate and rhythm: Frequent: palpitation. Infrequent: tachycardia. Rare: bradycardia.

Metabolic and nutritional disorders: Infrequent: thirst and dehydration. Rare: hypocalcemia and hypoglycemia.

Special senses, other disorders: Infrequent: taste perversion.

Urinary system disorders: Infrequent: micturition frequency and polyuria. Rare: nocturia, renal pain and abnormal urine.

Cardiovascular disorders, general: Infrequent: abnormal ECG.

Platelet, bleeding and clotting disorders: Infrequent: epistaxis. Rare: purpura.

Autonomic nervous system: Rare: syncope.

Postmarketing Experience

Because these events are reported voluntarily from a population of uncertain size, it is not always possible to reliably estimate their frequency. Information is often incomplete so that a definite causal relationship to drug exposure can often not be established.

Central and peripheral nervous system: Seizure.

DRUG ABUSE AND DEPENDENCE

Although the abuse potential of FROVA has not been specifically assessed in clinical trials, no abuse of, tolerance to, withdrawal from, or drug-seeking behavior was observed in patients who received FROVA. The 5-HT1 agonists, as a class, have not been associated with drug abuse.

OVERDOSAGE

There is no direct experience of any patient taking an overdose of FROVA. The maximum single dose of frovatriptan given to male and female patients with migraine was 40 mg (16 times the clinical dose) and the maximum single dose given to healthy male subjects was 100 mg (40 times the clinical dose) without significant adverse events.

As with other 5-HT1 receptor agonists, there is no specific antidote for frovatriptan. The elimination half-life of frovatriptan is 26 hours, therefore if overdose occurs, the patient should be monitored closely for at least 48 hours and be given any necessary symptomatic treatment.

The effects of hemo- or peritoneal dialysis on blood concentrations of frovatriptan are unknown.

DOSAGE AND ADMINISTRATION

The recommended dose is a single tablet of FROVA (frovatriptan 2.5 mg) taken orally with fluids.

If the headache recurs after initial relief, a second tablet may be taken, providing there is an interval of at least 2 hours between doses. The total daily dose of frovatriptan should not exceed 3 tablets (3 x 2.5 mg per day).

There is no evidence that a second dose of frovatriptan is effective in patients who do not respond to a first dose of the drug for the same headache.

The safety of treating an average of more than 4 migraine attacks in a 30-day period has not been established.

HOW SUPPLIED

FROVA tablets, containing 2.5 mg of frovatriptan (base) as the succinate, are available as round, white, film-coated tablets debossed with 2.5 on one side and “E” on the other side. The tablets are available in:

Blister card of 9 tablets, 1 blister card per carton (NDC 63481-025-09)

Store at controlled room temperature, 25°C (77°F) excursions permitted to 15 - 30°C (59°F - 86°F) [see USP Controlled Room Temperature]. Protect from moisture.

U.S. Patent Nos 5,962,501, 5,827,871, 5,637,611 and 5,464,864 and 5,616,603.

Rx Only

Manufactured for:
Endo Pharmaceuticals Inc.
Chadds Ford, PA 19317

Manufactured by:
Almac Pharma Services Limited
Craigavon, BT63 5UA, UK

FROVA is a registered trademark of Vernalis Development Limited.

© 2007 Endo Pharmaceuticals Inc. PX544-3 / April, 2007

PATIENT INFORMATION

PATIENT INFORMATION: The following wording is contained in a separate leaflet provided for patients.

PATIENT INFORMATION ABOUT
FROVA® (frovatriptan succinate) Tablets

Read this information before you start taking FROVA (FRO-va). Also, read the information each time you renew your prescription, in case anything has changed. This leaflet does not contain all of the information about FROVA. For further information or advice ask your doctor or pharmacist. You and your doctor should discuss FROVA before you start taking the medicine and at regular checkups.

What is FROVA?

FROVA is a prescription medicine used to treat migraine attacks in adults. It is in the class of drugs called selective serotonin receptor agonists.

FROVA should only be taken for a migraine headache. Do not use FROVA to treat headaches that might be caused by other conditions. Tell your doctor about your symptoms. Your doctor will decide if you have migraine headaches and if FROVA is for you.

There is more information about migraine at the end of this leaflet.

Who should not take FROVA?

Do not take FROVA if you:

- have uncontrolled high blood pressure
- have heart disease or a history of heart disease
- have hemiplegic or basilar migraine (if you are not sure about this, ask your doctor)
- have had a stroke
- have circulation (blood flow) problems
- have taken a similar drug (a serotonin receptor agonist) in the last 24 hours. These include sumatriptan (IMITREX®), naratriptan (AMERGE™), zolmitriptan (ZOMIG™), rizatriptan (MAXALT™), eletriptan hydrobromide (RELPAX®),or almotriptan (AXERT™)
- have taken ergotamine type medicines in the last 24 hours. These include BELLERGAL®, CAFERGOT®, ERGOMAR®, WIGRAINE®, DHE 45®, or SANSERT®
- have any allergic reaction to the tablet

What you should tell your doctor before and during treatment with FROVA?

To help your doctor decide if FROVA is right for you, tell your doctor if you:

- are pregnant, or planning to become pregnant
- are breast-feeding or plan to breast-feed
- have any history of chest pain, shortness of breath, or palpitations
- have any risk factors for heart disease, including
  - high blood pressure
  - diabetes
  - high cholesterol
  - overweight
  - smoking
  - a family history of heart disease
  - past menopause
  - male over 40 years old
- are taking any other medicines, including prescription and non-prescription medicines, and herbal supplements
- have any past or present medical problems
- have previous allergies to any medicine

Tell your doctor if you take

- propranolol
- selective serotonin reuptake inhibitors (SSRIs) or serotonin norepinephrine reuptake inhibitors (SNRIs), two types of drugs for depression or other disorders. Common SSRIs are CELEXA® (citalopram HBr), LEXAPRO® (escitalopram oxalate), PAXIL® (paroxetine), PROZAC®/SARAFEM® (fluoxetine), SYMBYAX® (olanzapine/fluoxetine), ZOLOFT® (sertraline), and fluvoxamine. Common SNRIs are CYMBALTA® (duloxetine) and EFFEXOR® (venlafaxine).

These medicines may affect how FROVA works, or FROVA may affect how these medicines work.

How should you take FROVA?

Take one FROVA tablet anytime after the start of your migraine headache. If your headache comes back after your first dose, you may take a second tablet after two (2) hours. Do not take more than three (3) FROVA tablets in a 24-hour period.

If you take too much medicine, contact your doctor, hospital emergency department, or poison control center right away.

What are the common side effects of FROVA?

The most common side effects associated with use of FROVA are:

- dizziness
- fatigue (tiredness)
- headache (other than a migraine headache)
- paresthesia (feeling of tingling)
- dry mouth
- flushing (hot flashes)
- feeling hot or cold
- chest pain
- dyspepsia (indigestion)
- skeletal pain (pain in joints or bones)

Tell your doctor about any symptoms that you develop while taking FROVA. If you feel dizziness or fatigue, take extra care or avoid driving and operating machinery.

In very rare cases, patients taking this class of medicines experience serious heart problems, stroke, or increased blood pressure. If you develop pain, tightness, heaviness, or pressure in your chest, throat, neck, or jaw, contact your doctor right away.

Also contact your doctor right away if you develop a rash or itching after taking FROVA. You may be allergic to this medicine.

What is a migraine and how does it differ from other headaches?

Migraine is an intense, throbbing headache that often affects one side of the head. It often includes nausea, vomiting, and sensitivity to light and sound. The pain and symptoms from a migraine headache may be worse than the pain and symptoms of a common headache. Migraine headaches usually last for hours or longer.

Some people have problems with vision (an aura) before they get a migraine headache. These include flashing lights, wavy lines, and dark spots.

Only your doctor can determine that your headache is a migraine headache, so it is important that you discuss all of your symptoms with your doctor.

LEXAPRO® / CELEXA® are registered trademarks of Forest Pharmaceuticals, Inc.

PAXIL® is a registered trademark of GlaxoSmithKline.

PROZAC® / SARAFEM® / SYMBYAX® / CYMBALTA® are registered trademarks of Eli Lilly and Company

ZOLOFT® is a registered trademark of Pfizer Pharmaceuticals.

EFFEXOR® is a registered trademark of Wyeth Pharmaceuticals.

FROVA is a registered trademark of Vernalis Development Limited.

© 2007 Endo Pharmaceuticals Inc. PX544-3 / April, 2007

FROVA 2.5MG LABEL IMAGE